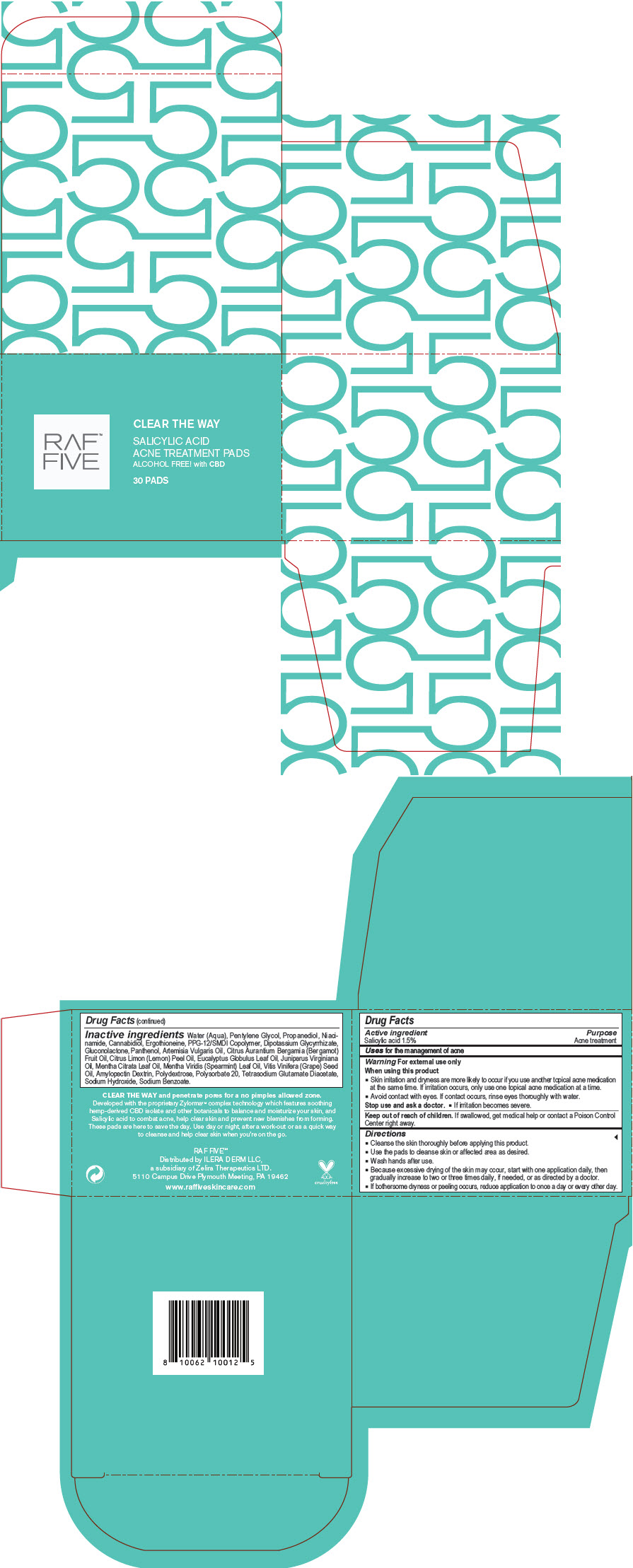 DRUG LABEL: RAF Five - Clear the Way Salicylic Acid Acne Treatment Pads
NDC: 66163-4456 | Form: LIQUID
Manufacturer: Cosmetic Solutions LLC
Category: otc | Type: HUMAN OTC DRUG LABEL
Date: 20210826

ACTIVE INGREDIENTS: salicylic acid 1.5 g/1 1
INACTIVE INGREDIENTS: Water; Pentylene Glycol; Propanediol; Niacinamide; Cannabidiol; Ergothioneine; PPG-12/SMDI Copolymer; Glycyrrhizinate Dipotassium; Gluconolactone; Panthenol; Artemisia Vulgaris Top Oil; Bergamot Oil; Lemon Oil, Cold Pressed; Eucalyptus Oil; Juniperus Virginiana Oil; SPEARMINT OIL; Grape Seed Oil; Polydextrose; Polysorbate 20; Tetrasodium Glutamate Diacetate; Sodium Hydroxide; Sodium Benzoate

RAF™ Five - Clear the Way Salicylic Acid Acne Treatment Pads

Drug Facts

Active ingredient

Salicylic acid 1.5%

Purpose

Acne treatment

Uses

for the management of acne

Warning

For external use only

When using this product

- Skin irritation and dryness are more likely to occur if you use another topical acne medication at the same time. If irritation occurs, only use one topical acne medication at a time.
- Avoid contact with eyes. If contact occurs, rinse eyes thoroughly with water.

Stop use and ask a doctor.

- If irritation becomes severe.

Keep out of reach of children. If swallowed, get medical help or contact a Poison Control Center right away.

Directions

- Cleanse the skin thoroughly before applying this product.
- Use the pads to cleanse skin or affected area as desired.
- Wash hands after use.
- Because excessive drying of the skin may occur, start with one application daily, then gradually increase to two or three times daily, if needed, or as directed by a doctor.
- If bothersome dryness or peeling occurs, reduce application to once a day or every other day.

Inactive ingredients

Water (Aqua), Pentylene Glycol, Propanediol, Niacinamide, Cannabidiol, Ergothioneine, PPG-12/SMDI Copolymer, Dipotassium Glycyrrhizate, Gluconolactone, Panthenol, Artemisia Vulgaris Oil, Citrus Aurantium Bergamia (Bergamot) Fruit Oil, Citrus Limon (Lemon) Peel Oil, Eucalyptus Globulus Leaf Oil, Juniperus Virginiana Oil, Mentha Citrata Leaf Oil, Mentha Viridis (Spearmint) Leaf Oil, Vitis Vinifera (Grape) Seed Oil, Amylopectin Dextrin, Polydextrose, Polysorbate 20, Tetrasodium Glutamate Diacetate, Sodium Hydroxide, Sodium Benzoate.

Distributed by ILERA DERM LLC,
a subsidiary of Zelira Therapeutics LTD.
5110 Campus Drive Plymouth Meeting, PA 19462

PRINCIPAL DISPLAY PANEL - 30 Pads Jar Carton

RAF™
FIVE

CLEAR THE WAY

SALICYLIC ACID
ACNE TREATMENT PADS
ALCOHOL FREE! with CBD

30 PADS